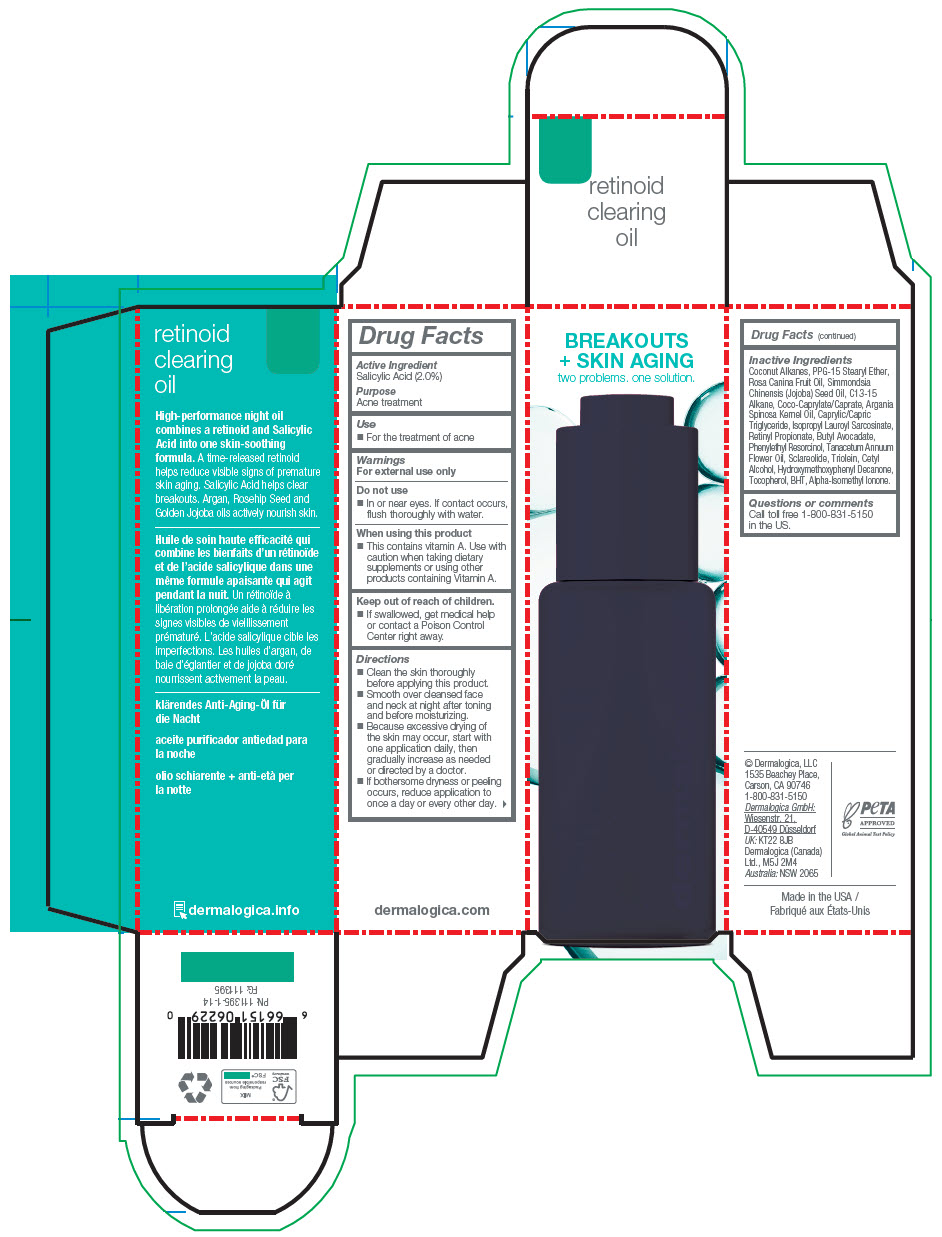 DRUG LABEL: RETINOID CLEARING
NDC: 68479-041 | Form: OIL
Manufacturer: Dermalogica, LLC.
Category: otc | Type: HUMAN OTC DRUG LABEL
Date: 20241021

ACTIVE INGREDIENTS: Salicylic Acid 2 mg/100 mL
INACTIVE INGREDIENTS: Coconut Alkanes; POLYPROPYLENE GLYCOL 15 STEARYL ETHER; Rosa Canina Fruit Oil; JOJOBA OIL; C13-15 Alkane; COCOYL CAPRYLOCAPRATE; ARGAN OIL; MEDIUM-CHAIN TRIGLYCERIDES; Isopropyl Lauroyl Sarcosinate; GLYCERYL TRIOLEATE; Butyl Avocadate; Cetyl Alcohol; Retinyl Propionate; Phenylethyl Resorcinol; Sclareolide; TANACETUM ANNUUM FLOWERING TOP OIL; 1-(4-HYDROXY-3-METHOXYPHENYL)-DECAN-3-ONE; BUTYLATED HYDROXYTOLUENE; Tocopherol

RETINOID CLEARING OIL

Drug Facts

Active Ingredient

Salicylic Acid (2.0%)

Purpose

Acne treatment

Use

- For the treatment of acne

Warnings

For external use only

Do not use

- In or near eyes. If contact occurs, flush thoroughly with water.

When using this product

- This contains vitamin A. Use with caution when taking dietary supplements or using other products containing Vitamin A.

Keep out of reach of children.

- If swallowed, get medical help or contact a Poison Control Center right away.

Directions

- Clean the skin thoroughly before applying this product.
- Smooth over cleansed face and neck at night after toning and before moisturizing.
- Because excessive drying of the skin may occur, start with one application daily, then gradually increase as needed or directed by a doctor.
- If bothersome dryness or peeling occurs, reduce application to once a day or every other day.

Inactive Ingredients

Coconut Alkanes, PPG-15 Stearyl Ether, Rosa Canina Fruit Oil, Simmondsia Chinensis (Jojoba) Seed Oil, C13-15 Alkane, Coco-Caprylate/Caprate, Argania Spinosa Kernel Oil, Caprylic/Capric Triglyceride, Isopropyl Lauroyl Sarcosinate, Retinyl Propionate, Butyl Avocadate, Phenylethyl Resorcinol, Tanacetum Annuum Flower Oil, Sclareolide, Triolein, Cetyl Alcohol, Hydroxymethoxyphenyl Decanone, Tocopherol, BHT, Alpha-Isomethyl Ionone.

Questions or comments

Call toll free 1-800-831-5150 in the US.

PRINCIPAL DISPLAY PANEL - 30 mL Bottle Carton

BREAKOUTS
+ SKIN AGING
two problems. one solution.